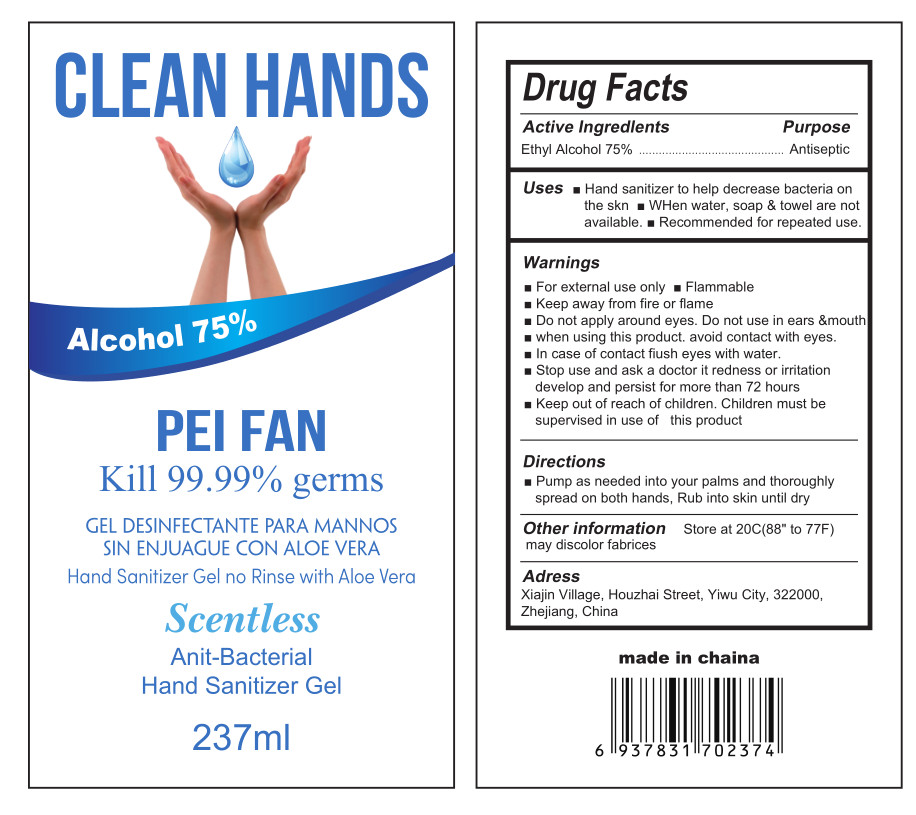 DRUG LABEL: Hand Sanitizer Gel
NDC: 52687-003 | Form: GEL
Manufacturer: Yiwu Kejing Cleaning Products Factory
Category: otc | Type: HUMAN OTC DRUG LABEL
Date: 20200430

ACTIVE INGREDIENTS: ALCOHOL 177.75 mL/237 mL
INACTIVE INGREDIENTS: WATER

DOSAGE AND ADMINISTRATION

Store at 20C(88" to 77F)

keep out of reach of children section

WARNINGS

■For external use only

■Flammable

■Keep away from fire or flame
■Do not apply around eyes. Do not use in ears &mouth
■when using this product. avoid contact with eyes.
■In case of contact fiush eyes with water.
■Stop use and ask a doctor it redness or iritation develop and persist for more than 72 hours
■Keep out of reach of children. Children must be supervised in use of this product

PURPOSE

Disinfection
Sterilization
No Rinseing

ACTIVE INGREDIENT

Alcohol

INACTIVE INGREDIENT

water

INDICATIONS AND USAGE

Pump as needed into your palms and thoroughly spread on both hands, Rub into skin until dry